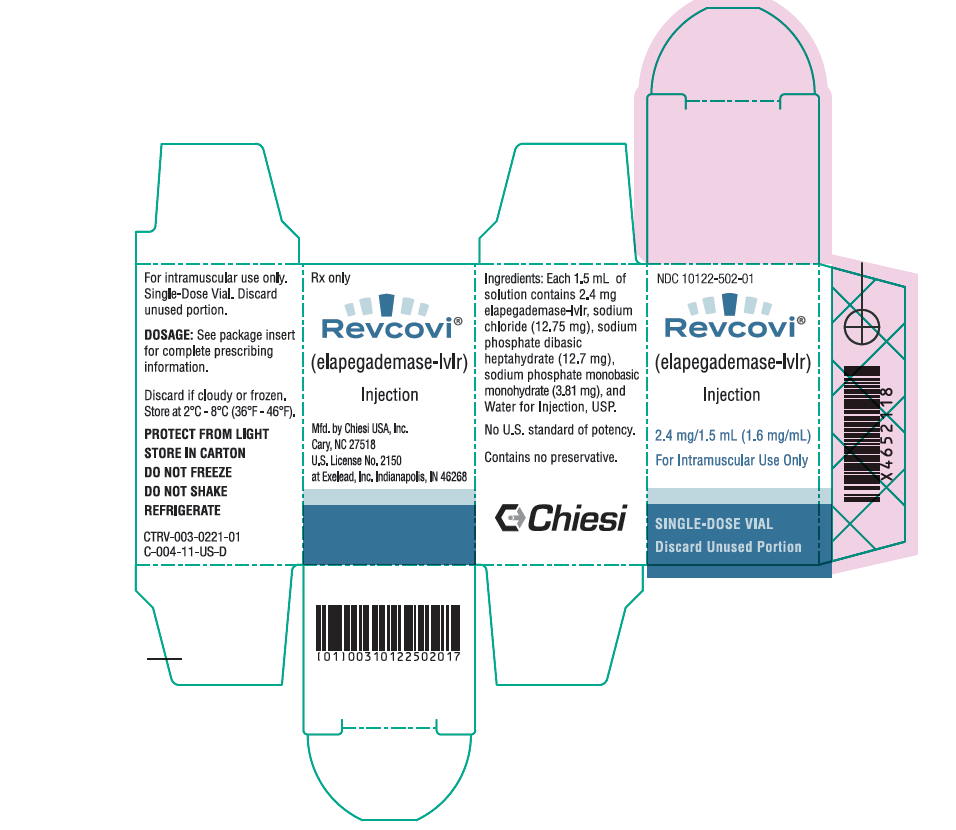 DRUG LABEL: Revcovi
NDC: 10122-502 | Form: INJECTION
Manufacturer: Chiesi USA, Inc.
Category: prescription | Type: HUMAN PRESCRIPTION DRUG LABEL
Date: 20220831

ACTIVE INGREDIENTS: ELAPEGADEMASE 1.6 mg/1 mL
INACTIVE INGREDIENTS: SODIUM CHLORIDE; SODIUM PHOSPHATE, DIBASIC, HEPTAHYDRATE; SODIUM PHOSPHATE, MONOBASIC, MONOHYDRATE; WATER

HIGHLIGHTS OF PRESCRIBING INFORMATION

These highlights do not include all the information needed to use REVCOVI® safely and effectively. See full prescribing information for REVCOVI.
REVCOVI (elapegademase-lvlr) injection, for intramuscular use
Initial U.S. Approval: 2018

RECENT MAJOR CHANGES

Dosage and Administration, Recommended Dosage | 12/2020

1 INDICATIONS AND USAGE

REVCOVI is a recombinant adenosine deaminase indicated for the treatment of adenosine deaminase severe combined immune deficiency (ADA-SCID) in pediatric and adult patients. (1)

2 DOSAGE AND ADMINISTRATION

- Patients transitioning from Adagen to REVCOVI: The starting dose of REVCOVI is 0.2 mg/kg weekly, intramuscularly. See Full Prescribing Information (FPI) for conversion formula from Adagen to REVCOVI. (2.1)

- Adagen-naïve patients: The starting dose of REVCOVI is 0.4 mg/kg weekly based on ideal body weight or actual weight whichever is greater, divided into two doses (0.2 mg/kg twice a week), intramuscularly. (2.1)
- For complete information, maintenance dosing and therapeutic monitoring, see FPI. (2.1, 2.3)
- REVCOVI is for intramuscular injection only. See FPI for administration instructions. (2.2)

3 DOSAGE FORMS AND STRENGTHS

Injection: 2.4 mg/1.5 mL (1.6 mg/mL) in a single-dose vial. (3)

4 CONTRAINDICATIONS

None (4)

5 WARNINGS AND PRECAUTIONS

- Injection Site Bleeding in Patients with Thrombocytopenia: Increased risk of local bleeding in patients with thrombocytopenia; should not be used if thrombocytopenia is severe. (5.1)
- Delay in Improvement of Immune Function: Protect immune deficient patients from infections until improvement in immune function. (5.2)

6 ADVERSE REACTIONS

The most common adverse reactions reported were cough (50%) and vomiting (33%). (6.1)

To report SUSPECTED ADVERSE REACTIONS, contact Chiesi USA, Inc. at 1-888-661-9260 or FDA at 1-800-FDA-1088 or www.fda.gov/medwatch.

FULL PRESCRIBING INFORMATION

1 INDICATIONS AND USAGE

REVCOVI is indicated for the treatment of adenosine deaminase severe combined immune deficiency (ADA-SCID) in pediatric and adult patients.

2 DOSAGE AND ADMINISTRATION

2.1 Recommended Dosage

Patients transitioning from Adagen to REVCOVI

If a patient's weekly Adagen dose is unknown, or a patient's weekly Adagen dose is at or lower than 30 U/kg, the recommended minimum starting dose of REVCOVI is 0.2 mg/kg, intramuscularly, once a week.

If a patient's weekly Adagen dose is above 30 U/kg, an equivalent weekly REVCOVI dose (mg/kg) should be calculated using the following conversion formula:

REVCOVI dose in mg/kg = | Adagen dose in U/kg 150

Subsequent doses may be increased by increments of 0.033 mg/kg weekly if trough ADA activity is under 30 mmol/hr/L, trough deoxyadenosine nucleotides (dAXP) are above 0.02 mmol/L, and/or the immune reconstitution is inadequate based on the clinical assessment of the patient. The total weekly dose may be divided into multiple intramuscular (IM) administrations during a week.

Adagen-naïve patients

The starting weekly dose of REVCOVI is 0.4 mg/kg based on ideal body weight or actual weight whichever is greater, divided into two doses (0.2 mg/kg twice a week), intramuscularly, for a minimum of 12 to 24 weeks until immune reconstitution is achieved. After that, the dose may be gradually adjusted down to maintain trough ADA activity over 30 mmol/hr/L, trough dAXP level under 0.02 mmol/L, and/or to maintain adequate immune reconstitution based on clinical assessment of the patient.

The optimal long-term dose and schedule of administration should be established by the treating physician for each patient individually and may be adjusted based on the laboratory values for trough ADA activity, trough dAXP level, and/or on the treating physician's medical assessment of the patient's clinical status.

2.2 Administration Instructions

REVCOVI is for IM injection only. Follow sterile IM administration technique guidelines appropriate to the patient's age and anatomy (i.e. choice of needle gauge and length, site of administration). Take precautions not to inject into or near an artery or nerve. Alternate the injection site periodically.

Preparation of Injection and Procedure Instructions

- REVCOVI should not be diluted nor mixed with any other drug prior to administration.
- Visually inspect REVCOVI for particulate matter and discoloration prior to administration. REVCOVI is a clear, colorless solution; discard if solution is discolored, cloudy or contains particulate matter.
- Do not freeze or shake. REVCOVI should not be used if there are any indications that it may have been frozen. Once removed from refrigeration, allow REVCOVI to equilibrate to room temperature for 30 minutes.
- REVCOVI is to be administered using polypropylene syringes. Draw the solution from the vial with a 25- gauge needle or larger.
- Change the needle to a size and gauge appropriate for the patient's intramuscular administration.
- REVCOVI should be administered immediately after syringe preparation.
- Any remaining medication in the vial must be discarded immediately.

2.3 Therapeutic Monitoring Schedule

The treatment of ADA-SCID with REVCOVI should be monitored by measuring trough plasma ADA activity, trough dAXP levels, and/or total lymphocyte counts. Monitoring should be more frequent if therapy was interrupted or if an enhanced rate of clearance of plasma ADA activity develops.

Collect blood samples for the analysis of trough plasma ADA activity and trough dAXP level prior to the first administration of REVCOVI for the week.

ADA Activity

Once treatment with REVCOVI has been initiated, a target trough plasma ADA activity should be at least 30 mmol/hr/L. In order to determine an effective dose of REVCOVI, trough plasma ADA activity (pre-injection) should be determined every 2 weeks for Adagen-naïve patients and every 4 weeks for patients previously receiving Adagen therapy, during the first 8 - 12 weeks of treatment, and every 3 - 6 months thereafter.

A decrease of ADA activity below this level suggests noncompliance to treatment or a development of antibodies (anti-drug, anti-PEG, and neutralizing antibodies). Antibodies to REVCOVI should be suspected if a persistent fall in pre-injection levels of trough plasma ADA activity below 15 mmol/hr/L occurs. In such patients, testing for antibodies to REVCOVI should be performed.

If a persistent decline in trough plasma ADA activity occurs, immune function and clinical status should be monitored closely and precautions should be taken to minimize the risk of infection. If antibodies to REVCOVI are found to be the cause of a persistent fall in trough plasma ADA activity, then adjustment in the dosage of REVCOVI and other measures may be taken to induce tolerance and restore adequate ADA activity.

Erythrocyte dAXP

Two months after starting REVCOVI treatment, trough erythrocyte dAXP levels should be maintained below 0.02 mmol/L, and monitored at least twice a year.

Immune Function

The degree of immune function may vary from patient to patient. Each patient will require appropriate monitoring consistent with immunologic status. Total and subset lymphocytes should be monitored periodically as follows:

- Adagen-naïve patients: every 4 – 8 weeks for up to 1 year, and every 3 – 6 months thereafter
- Other patients: every 3 - 6 months

Immune function, including the ability to produce antibodies, generally improves after 2 - 6 months of therapy, and matures over a longer period. In general, there is a lag between the correction of the metabolic abnormalities and improved immune function. Improvement in the general clinical status of the patient may be gradual (as evidenced by improvement in various clinical parameters) but should be apparent by the end of the first year of therapy.

3 DOSAGE FORMS AND STRENGTHS

Injection: 2.4 mg/1.5 mL (1.6 mg/mL) clear and colorless solution of elapegademase-lvlr in a single-dose vial.

4 CONTRAINDICATIONS

None.

5 WARNINGS AND PRECAUTIONS

5.1 Injection Site Bleeding in Patients with Thrombocytopenia

Since REVCOVI is administered by IM injection, it should be used with caution in patients with thrombocytopenia and should not be used if thrombocytopenia is severe.

5.2 Delay in Improvement of Immune Function

Maintain precautions to protect immune deficient patients from infections until improvement in immune function has been achieved. The timing and degree of improvement in immune function may vary from patient to patient.

6 ADVERSE REACTIONS

6.1 Clinical Trials Experience

Because clinical trials are conducted under widely varying conditions, adverse reaction rates observed in the clinical trials of a drug cannot be directly compared to rates in the clinical trials of another drug and may not reflect the rates observed in practice.

REVCOVI was administered intramuscularly in two prospective, open-label, single-arm, multi‑center studies to evaluate efficacy, safety, tolerability, and pharmacokinetics in patients with ADA-SCID: Study 1 was performed in the US and Study 2 was performed in Japan [see Clinical Studies (14)]. Overall, 10 patients were treated and adverse reactions reported are summarized below.

Study 1

Study 1 is a one-way crossover study, conducted in the US, to evaluate the safety, efficacy, and pharmacokinetics of REVCOVI in patients with ADA‑SCID who were receiving therapy with Adagen. Six patients, 8 to 37 years of age enrolled in the study. Patients' exposure to REVCOVI ranged from 2 weeks to 146 weeks. No deaths were reported and one patient discontinued treatment due to injection site pain associated with an earlier drug product formulation that was consequently modified.

The most common adverse reactions were cough (3/6 patients) and vomiting (2/6 patients). Other adverse reactions that were reported in one patient each were: abdominal pain upper, arthralgia, asthenia, cerumen impaction, conjunctivitis, convulsion, dental caries, diarrhea, ear canal irritation, ear lobe infection, epistaxis, fatigue, fungal skin infection, gait disturbance, gastrointestinal infection, groin abscess, hematochezia, haemophilus infection (pulmonary), hemoptysis, influenza, injection site discomfort, laceration, lymphadenopathy, migraine, nasal edema, nausea, nephrolithiasis, oral candidiasis, oropharyngeal pain, otitis externa, productive cough, rash, stoma site infection, swelling face, tooth abscess, tooth extraction and upper respiratory tract infection, regardless of investigator causality assessment.

Study 2

Study 2 is a single-arm clinical study that was conducted to assess the safety, efficacy and pharmacokinetics of REVCOVI in patients with ADA-SCID. Four patients 3.4 months to 25 years of age, all Asian, were enrolled in the study and received REVCOVI. Three patients received REVCOVI for 21 weeks and one patient received REVCOVI for 15 weeks. One death due to CMV pneumonitis and respiratory failure was observed in an infant, who had also experienced pulmonary hemorrhage, respiratory failure and upper respiratory tract infection that represented serious adverse events. Neutropenia was a serious adverse reaction reported by one of the patients. There were 22 reported adverse events for four patients. Most common adverse events were respiratory infections (2/4 patients).

6.2 Immunogenicity

As with all therapeutic proteins, there is potential for immunogenicity. The immunogenicity results from Study 1 and Study 2 suggest that patients who previously received Adagen may present an immunologic response to REVCOVI. Therefore, monitoring for changes in ADA levels during REVCOVI treatment is recommended. [see Dosage and Administration (2.3)]

The observed incidence of antibodies (including neutralizing antibodies) is dependent on assay sensitivity and specificity, assay methodology, and concomitant medications. Therefore, the comparison of the incidence of antibodies to REVCOVI with the incidence of antibodies to other products may be misleading.

6.3 Postmarketing Experience with ADAGEN

The following postmarketing adverse reactions were voluntarily reported for Adagen, the same class of enzyme replacement therapy used in the treatment of ADA-SCID, and may also be seen with REVCOVI treatment:

- Hematologic: hemolytic anemia, auto-immune hemolytic anemia, thrombocythemia, thrombocytopenia and autoimmune thrombocytopenia
- Dermatological: injection site erythema, urticaria
- Lymphomas

Since these reactions are reported voluntarily from a population of uncertain size, it is not always possible to reliably estimate their frequency or establish a causal relationship to drug exposure.

7 DRUG INTERACTIONS

The drug interaction potential of REVCOVI is not known.

8 USE IN SPECIFIC POPULATIONS

8.1 Pregnancy

Risk Summary

Adequate and well-controlled studies with REVCOVI have not been conducted in pregnant women to inform a drug-associated risk. Animal reproduction studies have not been conducted with REVCOVI. It is not known whether REVCOVI can cause fetal harm when administered to a pregnant woman or can affect reproduction capacity.

All pregnancies have a risk of birth defect, loss, or other adverse outcomes. In the US general population, the estimated background risk of major birth defects and miscarriage in clinically recognized pregnancies is 2% to 4% and 15% to 20%, respectively.

Data

Human

No pregnancy was reported for any patients receiving REVCOVI. There are two reports of confirmed cases of successful pregnancy and delivery in ADA-SCID patients treated with Adagen (the same class of enzyme replacement therapy used in the treatment of ADA-SCID). No teratogenic effects of Adagen were reported.

For patients treated with REVCOVI, more frequent monitoring of the health status for both the mother during pregnancy and the development of the offspring is recommended.

8.2 Lactation

Risk Summary

Human or animal lactation studies have not been conducted to assess the presence of REVCOVI in breast milk, the effects on the breastfed infant, or the effects on milk production for the mother.

The developmental and health benefits of breastfeeding should be considered along with the mother's clinical need for REVCOVI and any potential adverse effects on the breastfed infant from REVCOVI or from the underlying maternal condition.

8.4 Pediatric Use

The safety and efficacy of REVCOVI have been established in pediatric patients [see Clinical Studies (14)].

8.5 Geriatric Use

REVCOVI was not studied in patients 65 years and older.

10 OVERDOSAGE

There are no reports of administration of REVCOVI in excess of the prescribed doses. The highest weekly prescribed dose administered in the clinical studies was 0.4 mg/kg. In nonclinical studies, there was no evidence of toxicity related to study drug at doses up to 1.8-fold the clinical dose (based on mean human AUC normalized to the dose of REVCOVI administered per patient), except for a slight increase in activated partial thromboplastin time (APTT).

11 DESCRIPTION

Elapegademase-lvlr is a recombinant adenosine deaminase (rADA) based on bovine amino acid sequence, conjugated to monomethoxypolyethylene glycol (mPEG). rADA is manufactured in E. coli and is covalently conjugated to mPEG with a succinimidyl carbamate linker to produce methoxypolyethylene glycol recombinant adenosine deaminase (SC-PEG rADA). The approximate molecular weight of elapegademase-lvlr (SC-PEG rADA) is 113 KDa.

REVCOVI (elapegademase-lvlr) injection is a sterile, preservative free, clear, colorless solution for intramuscular use supplied in single-dose vials. Each vial provides 1.5 mL of solution containing 2.4 mg elapegademase-lvlr (1.6 mg/mL), sodium chloride (12.75 mg), sodium phosphate dibasic heptahydrate (12.7 mg), sodium phosphate monobasic monohydrate (3.81 mg), and Water for Injection, USP. The pH is 6.9.

12 CLINICAL PHARMACOLOGY

12.1 Mechanism of Action

SCID associated with a deficiency of ADA enzyme is a rare, inherited, and often fatal disease. ADA enzyme is involved in purine metabolism, catalyzing the irreversible hydrolytic deamination of adenosine or deoxyadenosine to inosine or deoxyinosine, respectively, as well as several naturally occurring methylated adenosine compounds. Maintaining a low level of 2'-deoxyadenosine and adenosine is crucial for proper number and function of immune cells as well as decreasing the frequency of opportunistic infections. Elevated adenosine levels, as occurring in ADA deficiency, contribute to apoptosis and a block in the differentiation of thymocytes, causing severe T‑lymphopenia.

Elapegademase-lvlr provides an exogenous source of ADA enzyme that is associated with a decrease in toxic adenosine and deoxyadenosine nucleotides levels as well as an increase in lymphocyte number [see Clinical Studies (14)].

12.2 Pharmacodynamics

The effect of REVCOVI on the QT interval is not known.

12.3 Pharmacokinetics

The pharmacokinetics (PK) of REVCOVI were evaluated based on steady state plasma ADA activity in six patients with ADA-SCID (five adults and one pediatric) from two studies (Study 1 and Study 2) who received weekly IM injections at doses ranging from 4.99 to 19.6 mg [see Clinical Studies (14)]. The PK results are summarized in Table 1.

Table 1 Individual Estimates of Steady State Plasma Pharmacokinetic Parameters of REVCOVI Following Weekly IM Administration in ADA-SCID Patients
Study | Patient's Age (yrs), Sex, Race | Weekly Dose (mg) [mg/kg] | Tmax (hr) | DN AUC0-168hr (hr*mmol/hr/L)/ (mg/kg)b | DN Cmax (mmol/hr/L)/ (mg/kg)b | Ctrough (mmol/hr/L)c
Study 1a | 19, Male, Hispanic/Latino | 10.0 [0.188] | 47.7 | 32710 | 237 | 29.0
 | 21, Male, Hispanic/Latino | 10.2 [0.224] | 71.9 | 31343 | 219 | 37.7
 | 37, Male, Black/African American | 19.6 [0.2] | 48.2 | 42400 | 292 | 46.2
 | 30, Female, White/Caucasian | 10.0 [0.209] | 72.0 | 24564 | 166 | 23.5
Study 2a | 25, Male, Asian | 10.0 [0.167] | 48.0 | 37605 | 251 | 33.5
 | 16, Female, Asian | 4.99 [0.233] | 27.2 | 19013 | 150 | 20.2
a PK data calculated over the dosing interval after weekly IM administration of REVCOVI at a stable REVCOVI dose for at least five consecutive weeks
b Dose-normalized (DN) AUC0-168hr and Cmax estimates based on mg/kg/week dose of REVCOVI
c Non-dose normalized steady state Ctrough ADA activity in plasma at Day 7 prior to administration of next weekly dose

In Study 1, steady state ADA activity levels were reached following seven consecutive once weekly IM doses of REVCOVI. In addition, dAXP activity levels in all patients at the majority of all sampling timepoints in Study 1 were less than 0.02 mmol/L.

13 NONCLINICAL TOXICOLOGY

13.1 Carcinogenesis, Mutagenesis, Impairment of Fertility

Long-term studies in animals to evaluate carcinogenic potential or studies to evaluate mutagenic potential and impairment of fertility have not been performed with REVCOVI.

14 CLINICAL STUDIES

14.1 Study 1

Study 1, conducted in the US (NCT 01420627), is an ongoing Phase 3, open-label, multicenter, single-arm, one-way crossover study of REVCOVI. The purpose of this clinical study is to evaluate the safety, efficacy, and PK of REVCOVI in 6 patients with ADA-SCID, 4 males and 2 females, who are receiving therapy with Adagen. The study treatment consists of three phases: Adagen Lead-in Phase (minimum of 3 weeks), the REVCOVI Treatment Phase (weeks 1 through 21), and followed by the REVCOVI Maintenance Phase. Six patients treated in the study were 8 to 37 years of age at the start of the study. The starting weekly dose of REVCOVI was calculated based on the last Adagen dose received in the study. Weekly REVCOVI doses ranged from 0.188 mg/kg to 0.292 mg/kg [see Dosage and Administration (2.1)].

The efficacy endpoints assessed were as follows:

- Trough dAXP Level (metabolic detoxification was defined as a trough erythrocyte dAXP concentration equal to or below 0.02 mmol/L)
- Trough plasma ADA activity (adequate trough plasma ADA activity is defined as trough plasma ADA activity equal to or above 15 mmol/hr/L)
- Immune status (lymphocyte and B-, T-, and NK-lymphocyte subset counts as well as quantitative immunoglobulin [Ig] concentration [IgG, IgA, IgM])

A PK assessment was performed during Week 9 of the REVCOVI Treatment phase [see Clinical Pharmacology (12.3)].

Five of six patients reached the 21-week endpoint of the Treatment Phase, and three of six patients received treatment with REVCOVI (elapegademase-lvlr) for over 135 weeks. These patients (except for one value in a patient at Treatment Week 47) had erythrocyte dAXP concentration equal to or below 0.02 mmol/L. These patients had trough plasma ADA activity equal to or above 15 mmol/hr/L at 88/89 timepoints and maintained metabolic detoxification for at least 2 years under REVCOVI treatment. Patients achieved trough plasma ADA activity above 30 mmol/hr/L by week 5, except for one patient who achieved this level at week 1. The mean trough plasma ADA activity for patients receiving REVCOVI at a normalized dose of 0.2 mg/kg/week were 34.3 ± 6.6 mmol/hr/L. The same patients had a mean trough plasma ADA activity of 14.2 ± 5.1 mmol/hr/L when treated with Adagen at a normalized dose of 30 U/kg/week during the Lead-in Phase of the study.

Lymphocyte and subset counts during REVCOVI treatment increased above levels observed during the Adagen Lead-in Phase (i.e., PK day 1 or before the start of REVCOVI treatment): maximum increases of approximately 3-fold at Weeks 60-73 for one patient, maximum increases of approximately 2- to 3-fold at Weeks 73-99 for one patient and approximately 1.5- to 3-fold for the third patient at several timepoints. For these three patients who completed the primary endpoint (21 weeks of treatment) and received REVCOVI for over 135 weeks, a positive trend between high trough plasma ADA activity and increased total lymphocyte counts was observed.

Observations for the other three patients in the study, indicate that these patients also achieved complete detoxification based on trough dAXP level and trough plasma ADA activity, and show stable or slightly increased lymphocyte counts during REVCOVI treatment relative to values recorded during the Adagen Lead-in Phase.

14.2 Study 2

Study 2, conducted in Japan, is a single-arm clinical study that assessed the safety, efficacy and PK of REVCOVI in patients with ADA-SCID. The study includes two phases: 1) Evaluation, consisting of a Dose Adjustment Period (5 weeks) and a Dose Maintenance Period (16 weeks); and 2) Continuous Administration (Extension) Phase, to be continued until the end of the study.

A total of four patients were enrolled in the study: two males (age 25 years and 3.4 months) and two females (age 16 years and 4.3 months). Two patients, who were on Adagen treatment within 4 weeks before entering the study, received a first dose of REVCOVI that was calculated to be equivalent to the last Adagen dose received. One patient, who did not receive Adagen within four weeks prior to entering the study, was given the first dose of REVCOVI at 0.1 mg/kg body weight, followed by second and third doses at 0.133 mg/kg body weight and weekly thereafter. Over the dose adjustment phase of the study, the dose was titrated to meet criteria for dAXP level (equal to or below 0.02 mmol/L) and adequate trough ADA activity (equal to or above 15 mmol/hr/L). These three patients received REVCOVI for at least 21 weeks (having completed the 5-week Dosage Adjustment Period and the 16-week Maintenance Period) before entering the Extension Phase. The fourth patient (newly diagnosed Adagen-naïve patient with CMV pneumonia [see Adverse Reactions (6.1)]) was dosed with REVCOVI at 0.4 mg/kg weekly (divided into two IM administrations) for 16 weeks.

All four of the patients in Study 2 achieved and maintained detoxification (trough dAXP [erythrocyte or blood] ≤0.02 mmol/L) throughout their participation in the Treatment Phase of 21 weeks (Dose Adjustment and Dose Maintenance). Serum ADA activity increased after administering REVCOVI for all four patients, with three patients achieving activity level over 15 mmol/hr/L during the Dose Maintenance Period. Total lymphocyte counts and B-/T-/NK-lymphocyte subset counts for three patients increased from screening to Day 15 during dose adjustment and were stable or increasing during the Maintenance Period.

16 HOW SUPPLIED/STORAGE AND HANDLING

REVCOVI (elapegademase-lvlr) injection, 2.4 mg/1.5 mL (1.6 mg/mL), is a sterile, preservative free, clear, colorless solution for intramuscular use available as one single-dose vial per carton (NDC 10122-502-01).

The vial stopper is not made with natural rubber latex.

Single-dose vial; do not re-use the vial. Discard unused portions.

Store REVCOVI in the refrigerator between 2°C to 8°C (36°F to 46°F) in the original carton to protect from light. Do not freeze or shake. REVCOVI should not be used if there are any indications that it may have been frozen.

17 PATIENT COUNSELING INFORMATION

Importance of Compliance

Counsel patients and caregivers that continuous therapy and adherence to the recommended drug schedule is important for the success of the treatment.

Manufactured by: Chiesi USA, Inc. Cary, NC 27518, USA, U.S. License No. 2150 at Exelead Inc., 6925 Guion Rd, Indianapolis, IN 46268, USA

CTRV-001-1120-00-SPL-2

PRINCIPAL DISPLAY PANEL - 2.4 mg/1.5 mL Vial Carton

NDC10122-502-01

Revcovi®
(elapegademase-lvlr)
Injection

2.4 mg/1.5 mL (1.6 mg/mL)

For Intramuscular Use Only

SINGLE-DOSE VIAL

Discard Unused Portion